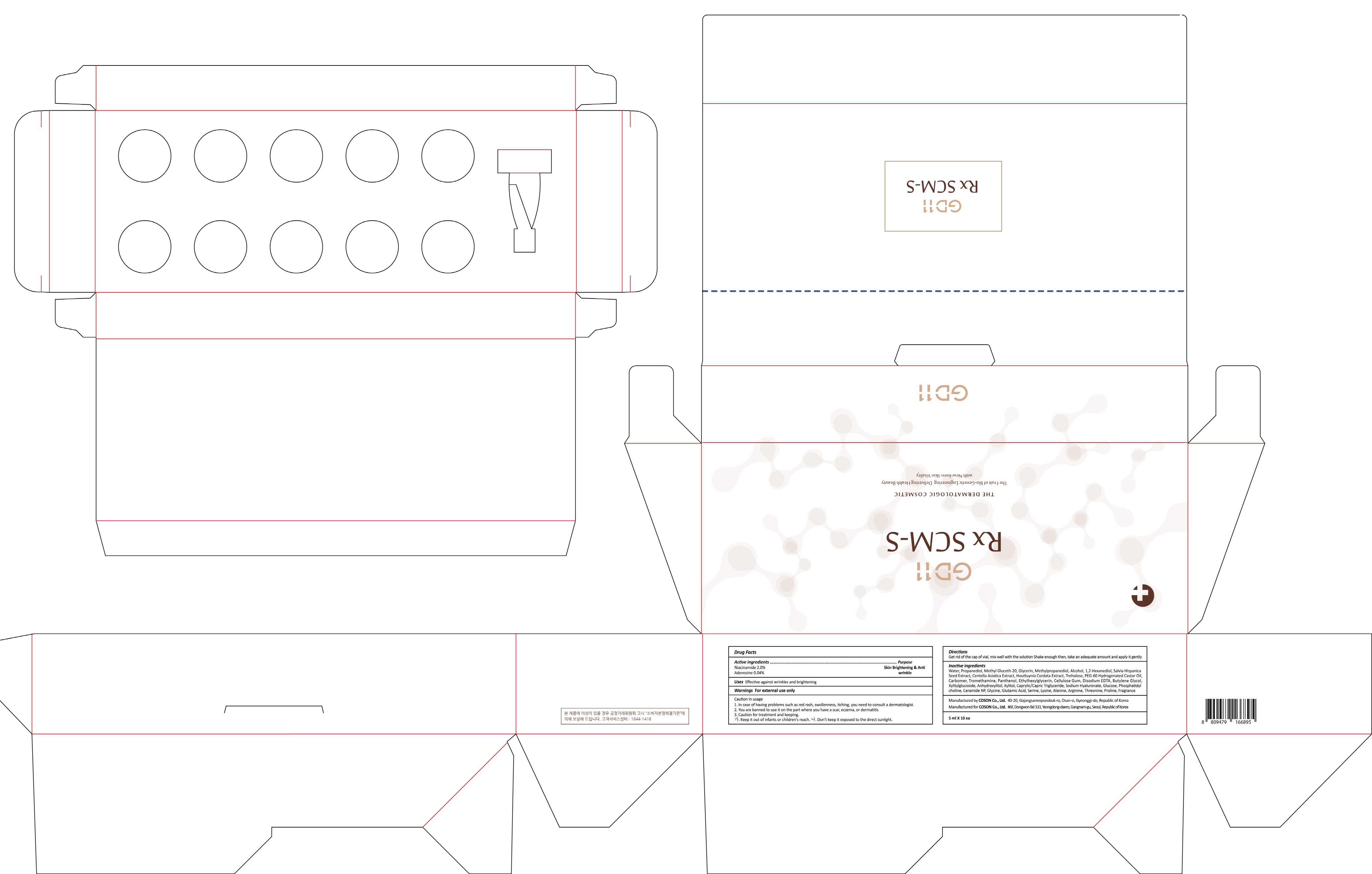 DRUG LABEL: GD11 Rx SCM S
NDC: 62171-090 | Form: LIQUID
Manufacturer: Coson Co., Ltd.
Category: otc | Type: HUMAN OTC DRUG LABEL
Date: 20170824

ACTIVE INGREDIENTS: Niacinamide 0.10 g/5 mL; Adenosine 0.002 g/5 mL
INACTIVE INGREDIENTS: Water; Propanediol

ACTIVE INGREDIENT

Active ingredients: Niacinamide 2.0%, Adenosine 0.04%

INACTIVE INGREDIENT

Inactive ingredients: Water, Propanediol, Methyl Gluceth-20, Glycerin, Methylpropanediol, Alcohol, 1,2-Hexanediol, Salvia Hispanica Seed Extract, Centella Asiatica Extract, Houttuynia Cordata Extract, Trehalose, PEG-60 Hydrogenated Castor Oil, Carbomer, Tromethamine, Panthenol, Ethylhexylglycerin, Cellulose Gum, Disodium EDTA, Butylene Glycol, Xylitylglucoside, Anhydroxylitol, Xylitol, Caprylic/Capric Triglyceride, Sodium Hyaluronate, Glucose, Phosphatidylcholine, Ceramide NP, Glycine, Glutamic Acid, Serine, Lysine, Alanine, Arginine, Threonine, Proline, Fragrance

PURPOSE

Purpose: Skin Brightening & Anti wrinkle

WARNINGS

Warnings: For external use only

Caution in usage 1. In case of having problems such as red rash, swollenness, itching, you need to consult a dermatologist. 2. You are banned to use it on the part where you have a scar, eczema, or dermatitis 3. Caution for treatment and keeping. - Keep it out of infants or children's reach. - Don't keep it exposed to the direct sunlight

KEEP OUT OF REACH OF CHILDREN

Keep it out of infants or children's reach.

Uses

Uses: Effective against wrinkles and brightening

Directions

Directions: Get rid of the cap of vial, mix well with the solution Shake enough then, take an adequate amount and apply it gently.